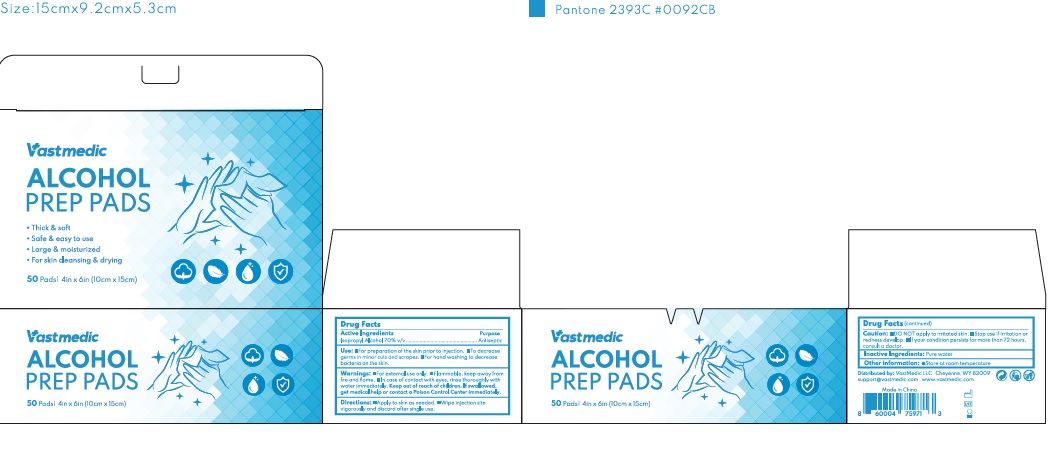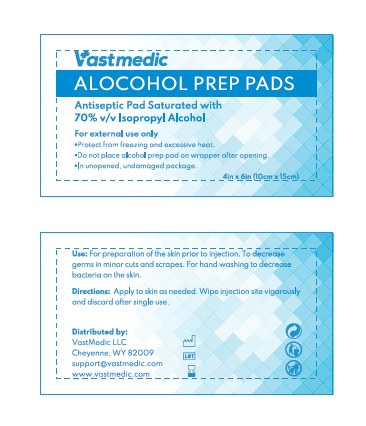 DRUG LABEL: Vastmedic ALCOHOL PREP PADS
NDC: 80227-002 | Form: CLOTH
Manufacturer: Vinedise LLC
Category: otc | Type: HUMAN OTC DRUG LABEL
Date: 20200904

ACTIVE INGREDIENTS: ISOPROPYL ALCOHOL 70 mL/100 mL
INACTIVE INGREDIENTS: WATER

VastMedic

Active Ingredients

Isopropyl Alcohol

Purpose

Antiseptic

Uses

- For preparation of the skin prior to injection.
- To decrease germs in minor cuts and scrapes.
- For hand washing to decrease bacteria on the skin.

Warnings

For external use only.

Flammable, keep away from fire and flame.

In case of contact with eyes, rinse thoroughly with water immediately.

Caution

DO NOT apply to irritated skin. Stop use if irritation or redness develop. If your condition persists for more than 72 hours, consult a doctor.

Direction

Apply to skin as needed. Wipe injection site vigorously and discard after single use.

Keep out of reach of children.

If swallowed, get medical help or contact a Poison Control Center immediately.

Other Information

Store at room temperature.

Inactive Ingredient

Purified water